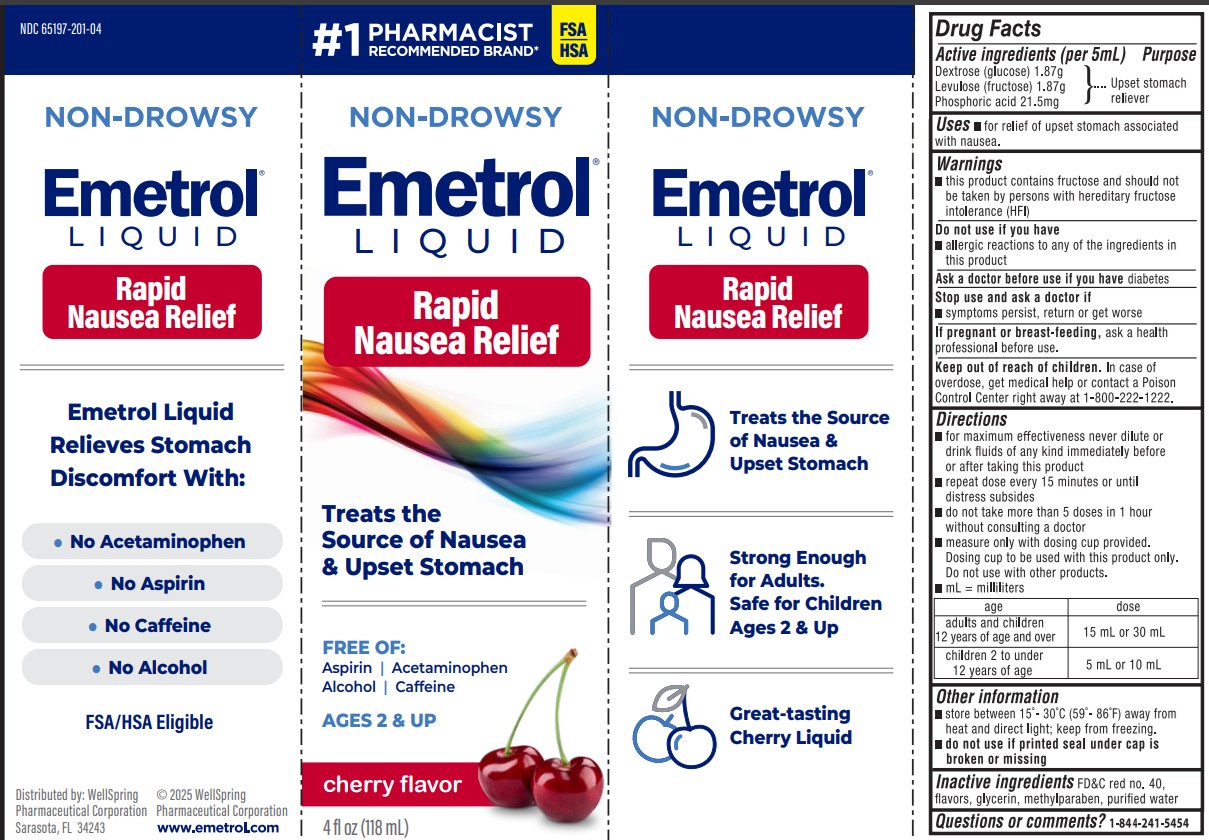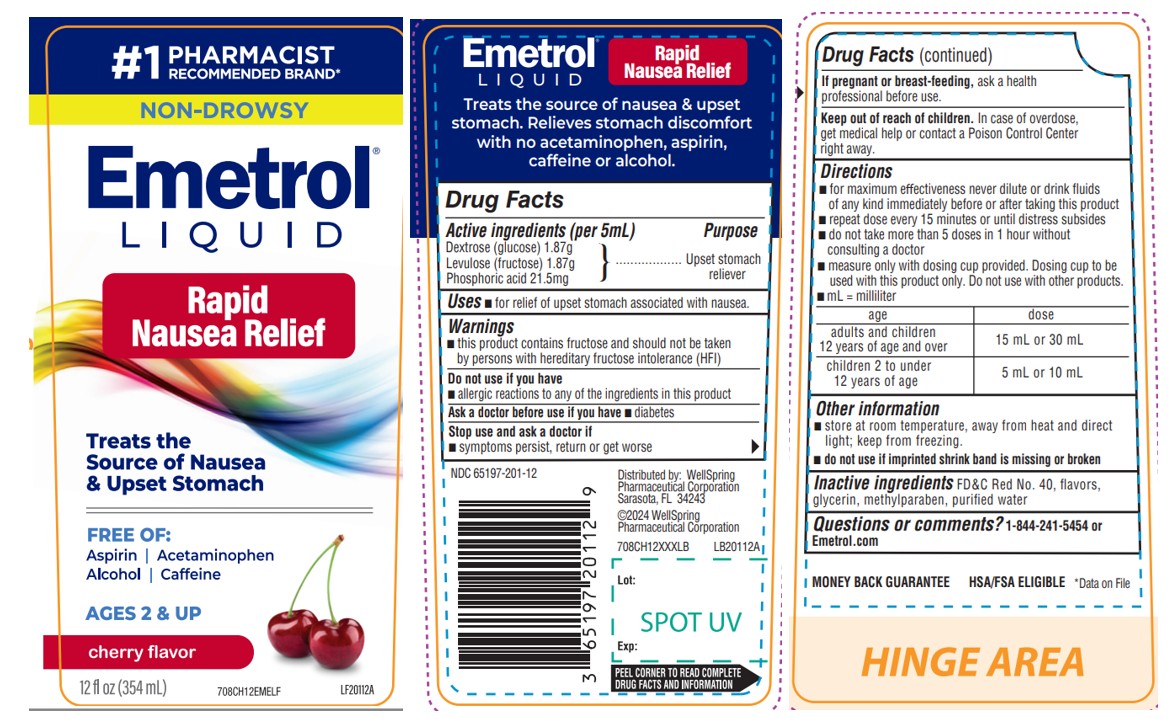 DRUG LABEL: Emetrol Cherry
NDC: 65197-201 | Form: SOLUTION
Manufacturer: WellSpring Pharmaceutical Corporation
Category: otc | Type: HUMAN OTC DRUG LABEL
Date: 20250610

ACTIVE INGREDIENTS: DEXTROSE 1.87 g/5 mL; PHOSPHORIC ACID 21.5 mg/5 mL; FRUCTOSE 1.87 g/5 mL
INACTIVE INGREDIENTS: FD&C RED NO. 40; WATER; GLYCERIN; METHYLPARABEN

Emetrol

Active ingredients

Phosphorated carbohydrate solution*
*each 5 mL contains:

- 1.87 g Dextrose (glucose)
- 1.87 g Levulose (fructose)
- 21.5 mg Phosphoric acid

Purpose

Upset Stomach Reliever

Uses

For relief of upset stomach associated with nausea due to overindulgence in food and drink.

Warnings

- This product contains fructose and should not be taken by persons with hereditary fructose intolerance (HFI).

Do not use if you have

- allergic reactions to any of the ingredients in this product

Ask a doctor before use if you have

- diabetes

Stop use and ask a doctor if

- symptoms persist, return or get worse

If pregnant or breast-feeding,

ask a health professional before use.

Keep out of reach of children.

In case of overdose, get medical help or contact a Poison Control Center right away. (1-800-222-1222)

Directions

- for maximum effectiveness never dilute or drink fluids of any kind immediately before or after taking this product
- adults and children 12 years of age and over: one to two tablespoons
- children 2 to under 12: one or two teaspoons
- repeat dose every 15 minutes or until distress subsides
- do not take more than 5 doses in 1 hour without consulting a doctor
- measure only with dosing cup provided. Dosing cup to be used with Emetrol only. Do not use with other products.

Other information

- Store between 20-25ºC (68-77ºF) away from heat and direct light; keep from freezing
- Do not use if printed foil seal under bottle cap is broken or missing

Inactive ingredients

FD&C red no. 40, flavors, glycerin, methylparaben, and purified water.

Questions or Comments?

call 1-844-241-5454

Distributed By

WellSpring Pharmaceutical Corporation
Sarasota, FL 34243 USA
(c) WellSpring 2019

PACKAGE LABEL

Emetrol Loquid Rapid Nausea Relief

Treats the source of Nausea & upset stomach

CT201048H
Emetrol 12 oz